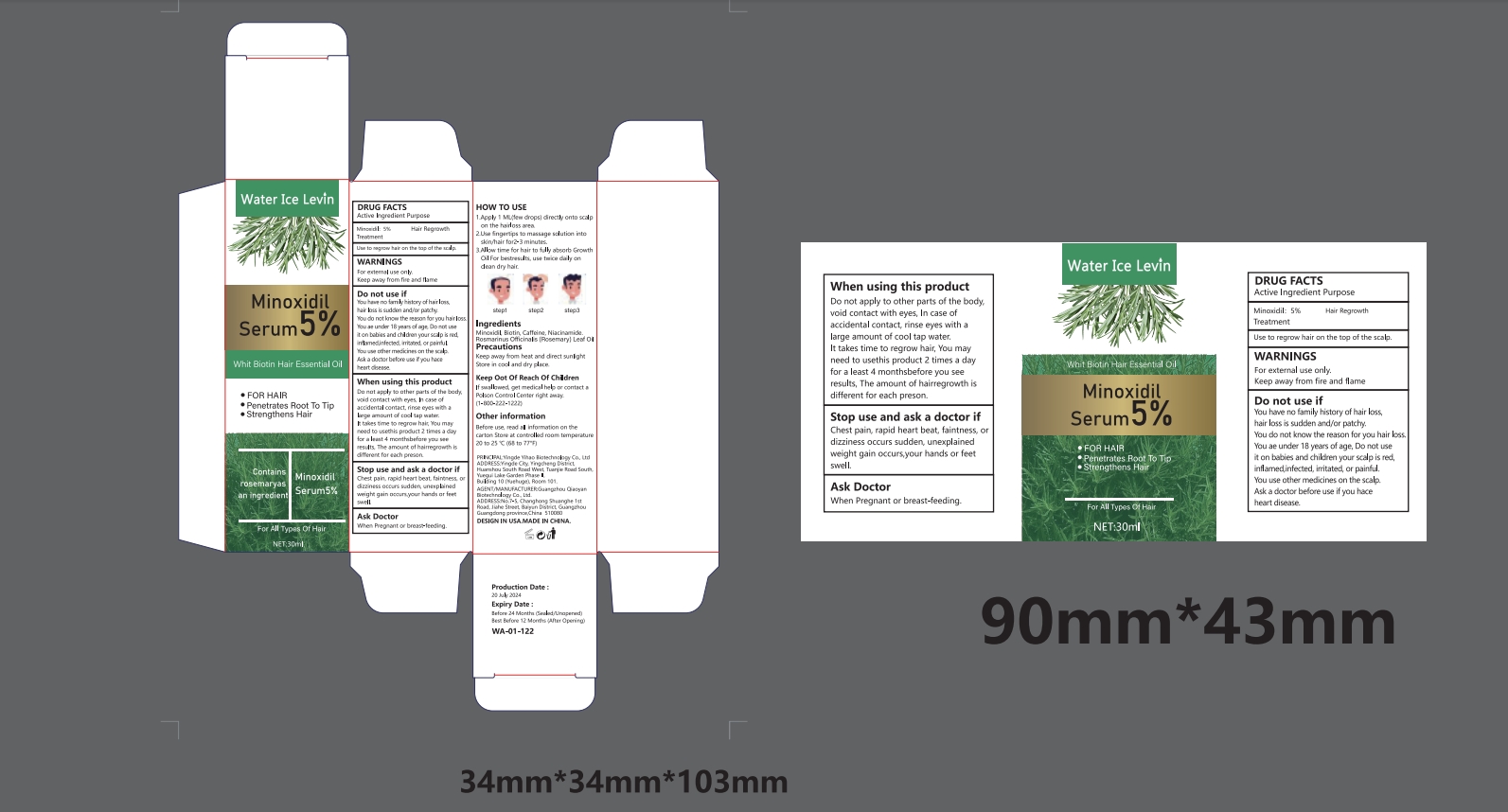 DRUG LABEL: Water lce Levin Whit Active Ingredient Purpose
NDC: 84550-003 | Form: LIQUID
Manufacturer: Guangzhou Qiaoyan Biotechnology Co.,Ltd.
Category: otc | Type: HUMAN OTC DRUG LABEL
Date: 20241101

ACTIVE INGREDIENTS: MINOXIDIL 5 g/5 g
INACTIVE INGREDIENTS: ROSMARINUS OFFICINALIS (ROSEMARY) LEAF OIL; BIOTIN; NIACINAMIDE; CAFFEINE

COMPONENTS

Minoxidil:5% Treatment
Hair Regrowth

PURPOSE

Use to regrow hair on the top of the scalp

STOP USE

Use to regrow hair on the top of the scalp

INDICATIONS AND USAGE

1.Apply 1 ML(few drops) directly onto scalp on the hairloss area.2.Use fingertips to massage solution into skin/hair for2-3 minutes.3.Allow time for hair to fully absorb Growth Oil For bestresults, use twice daily on clean dry hair.

WARNINGS

For external use only
Keep away from fire and flame

DOSAGE AND ADMINISTRATION

For external use only.

DO NOT USE

Do not apply to other parts of the body,void contact with eyes, In case of accidental contact, rinse eyes with a large amount of cool tap water.It takes time to regrow hair, You may need to usethis product 2 times a day for a least 4 monthsbefore you see results, The amount of hairregrowth is different for each preson.

WHEN USING

Do not apply to other parts of the body,void contact with eyes, In case of accidental contact, rinse eyes with a large amount of cool tap water.It takes time to regrow hair, You may need to usethis product 2 times a day for a least 4 monthsbefore you see results, The amount of hairregrowth is different for each preson.

STOP USE

Chest pain, rapid heart beat, faintness, or dizziness occurs sudden, unexplained weight gain occurs,your hands or feet swell.

KEEP OUT OF REACH OF CHILDREN

If swallowed, get medical help or contact a Polson Control Center right away.(1-800-222-1222)

INACTIVE INGREDIENT

biotin
Caffeine
Niacinamide